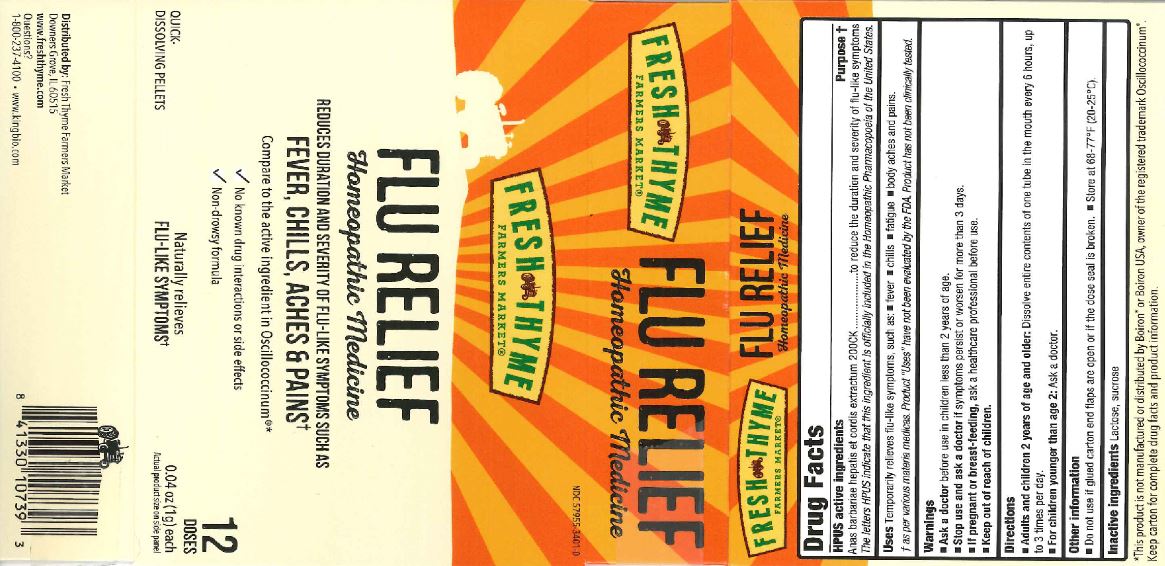 DRUG LABEL: Fresh Thyme Flu Relief
NDC: 57955-3401 | Form: PELLET
Manufacturer: King Bio Inc
Category: homeopathic | Type: HUMAN OTC DRUG LABEL
Date: 20180411

ACTIVE INGREDIENTS: CAIRINA MOSCHATA HEART/LIVER AUTOLYSATE 200 [hp_C]/1 g
INACTIVE INGREDIENTS: LACTOSE, UNSPECIFIED FORM; SUCROSE

Fresh Thyme Flu Relief

HPUS Active Ingredients

Anas barbariae hepatis et cordis extractum

The letters HPUS indicate that this ingredient is officially included in the Homeopathic Pharmacopoeia of the United States.

Purpose

Anas barbariae hepatis et cordis extractum...........to reduce the duration and severity of flu-like symptoms

Uses

Temporarily relieves flu-like symptoms, such as:

- fever
- chills
- faigue
- body aches and pains

as per various meteria medicas. Product "Uses" have not been evaluated by the FDA. Product has not been clinically tested.

Warnings

- Ask a doctor before use in children less than 2 years of age.
- Stop use and ask a doctor if symptoms persist or worsen for more than 3 days.
- If pregnant r breast-feeding, ask a healthcare professional before use.

- Keep out of reach of children.

Directions

Adults and children 2 years of age and older: Dissolve entire contents of one tube in the mouth every 6 hours, up to 3 times per day.

For children yunger than age 2: Ask a doctor.

Other Information

Do not use if glued end flaps are open or if the dose seal is broken

Store at 68-77°F (20-25°C)

Inactive Ingredients

Lactose, sucrose.